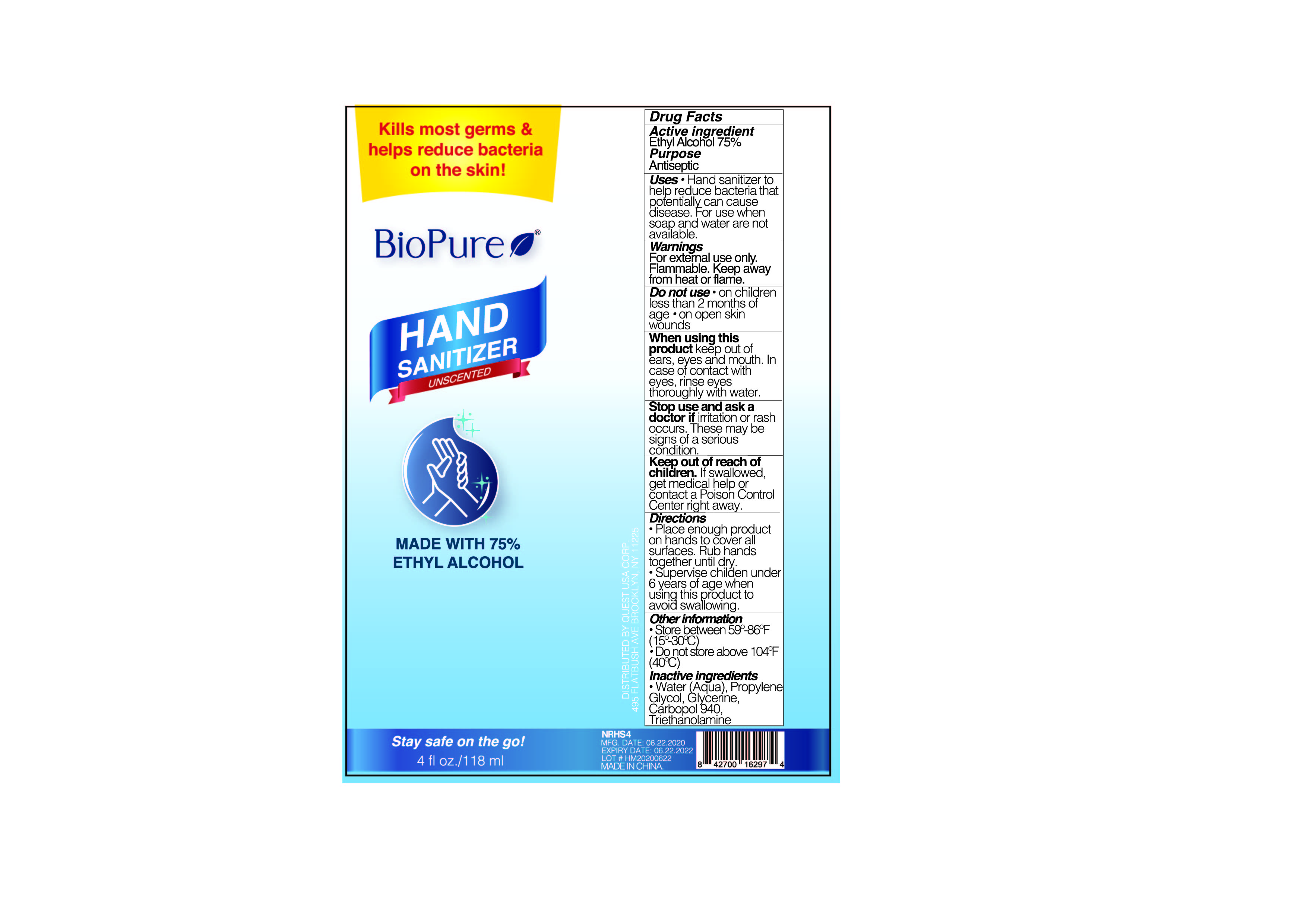 DRUG LABEL: Hand Sanitizer
NDC: 75427-001 | Form: GEL
Manufacturer: Jinhua City Wellmae Cosmetics Co., Ltd.
Category: otc | Type: HUMAN OTC DRUG LABEL
Date: 20220119

ACTIVE INGREDIENTS: ALCOHOL 75 mL/100 mL
INACTIVE INGREDIENTS: TROLAMINE; CARBOMER 940; PROPYLENE GLYCOL; GLYCERIN; WATER

75427-001
Hand sanitizer

Active Ingredient(s)

Ethyl Alcohol 75%

Purpose

Antiseptic

Use

Hand sanitizer to help reduce bacteria that potentially can cause disease. For use when soap and water are not available.

Warnings

For External Use Only. Flammable. Keep Away From Heat Or Flame.

Do not use

●ON CHILDREN LESS THAN 2 MONTHS OF AGE

●ON OPEN SKIN WOUNDS

WHEN USING

keep out of ears, eyes and mouth. In case of contact with eyes, rinse eyes thoroughly with water.

STOP USE

if iritation or rash occurs. These may be signs of a serious condition.

KEEP OUT OF REACH OF CHILDREN

If swallowed, get medical help or contract a Poison Control Center right away.

Directions

●Place enough product on hands to cover all surfaces. Rub hands together until dry.

●Supervise children under 6 years of age when using this product to avoid swallowing

Other information

●Store between 59°-86°F (15°-30℃)

●Do not store above 104°F (40℃)

Inactive ingredients

●Water (Aqua), Propylene Glycol, Glycerine, Carbopol 940, Triethanolamine